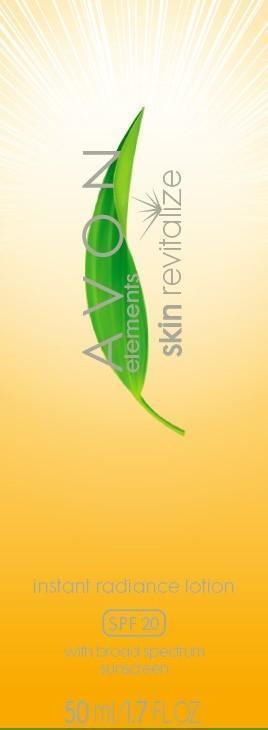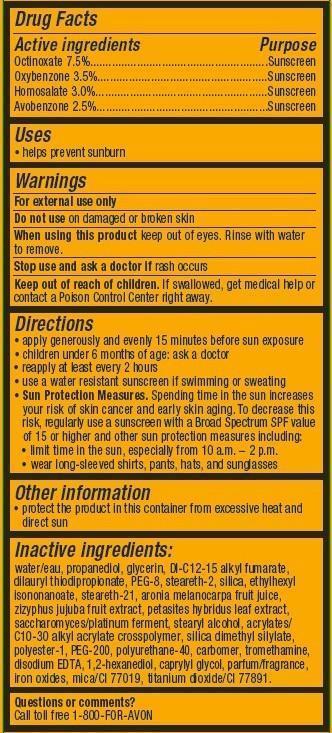 DRUG LABEL: Avon Elements
NDC: 10096-0302 | Form: LOTION
Manufacturer: New Avon LLC
Category: otc | Type: HUMAN OTC DRUG LABEL
Date: 20160219

ACTIVE INGREDIENTS: OCTINOXATE 75 mg/1 mL; OXYBENZONE 35 mg/1 mL; HOMOSALATE 30 mg/1 mL; AVOBENZONE 25 mg/1 mL

Active Ingredients
Octinoxate 7.5%.................................
Oxybenzone 3.5%..............................
Homosalate 3.0%...............................
Avobenzone 2.5%...............................

Purpose
............... Sunscreen
............... Sunscreen
.............. Sunscreen

.............. Sunscreen

Uses

- helps prevent sunburn

Warnings
For external use only

Do not use on damaged or broken skin

When using this product keep out of eyes. Rinse with water to remove.

Stop use and ask a doctor if rash occurs

Keep out of reach of children. If swallowed, get medical help or contact a Poison Control Center right away.

Directions

- apply generously and evenly 15 minutes before sun exposure
- children under 6 month of age:ask a doctor
- reapply at least every 2 hours
- use a water resistant sunscreen if swimming or sweating
- Sun Protection Measures. Spending time in the sun increases your risk of skin cancer and early skin aging. To decrease this risk, regularly use a sunscreen with a Broad Spectrum SPF value of 15 or higher and other sun protection measures including:
  • limit time in the sun, especially from 10 a.m. – 2 p.m.
  • wear long-sleeved shirts, pants, hats, and sunglasses

Other Information

- protect the product in this container from excessive heat and direct sun.

Inactive ingredients:
water/eau, propanediol, glycerin, DI-C12-15 alkyl fumarate, dilauryl thiodipropionate, PEG-8, steareth-2, silica, ethylhexyl isononanoate, steareth-21, aronia melanocarpa fruit juice, zizyphus jujuba fruit extract, petasites hybridus leaf extract, saccharomyces/platinum ferment, stearyl alcohol, acrylates/C10-30 alkyl acrylate crosspolymer, silica dimethyl silylate, polyester-1, PEG-200, polyurethane-40, carbomer, tromethamine, disodium EDTA, 1,2-hexanediol, caprylyl glycol, parfum/fragrance, iron oxides, mica/CI 77019, titanium dioxide/CI 77891.

Questions or comments?
Call toll free 1-800-FOR-AVON